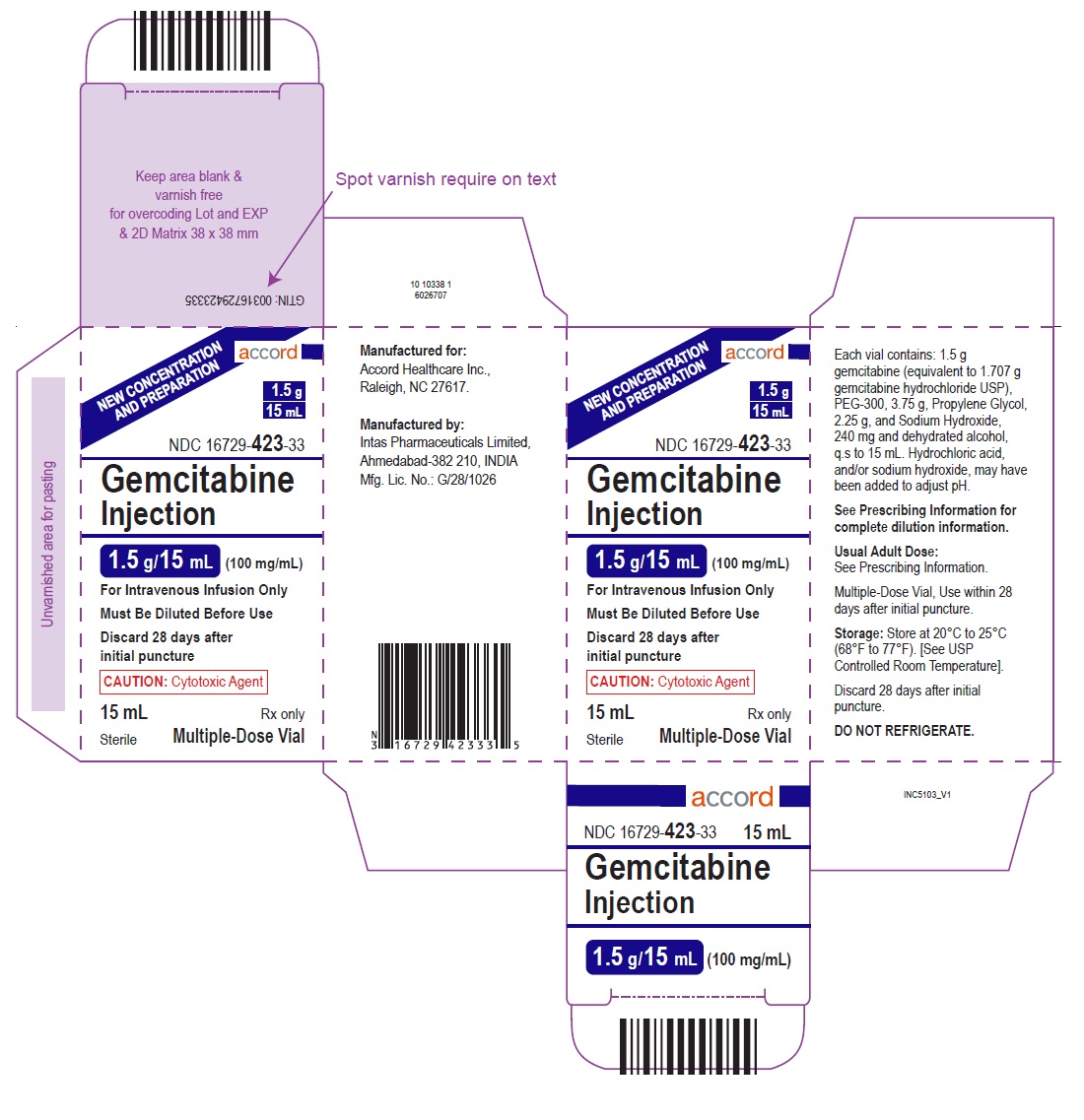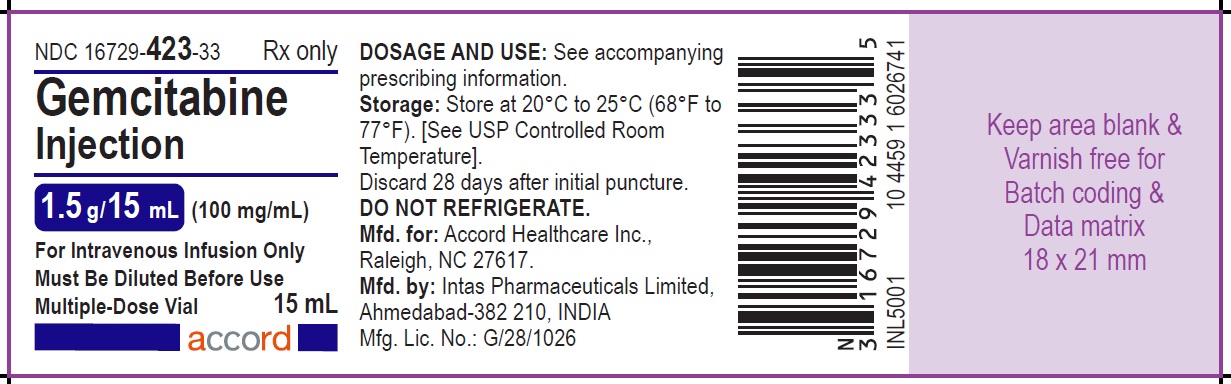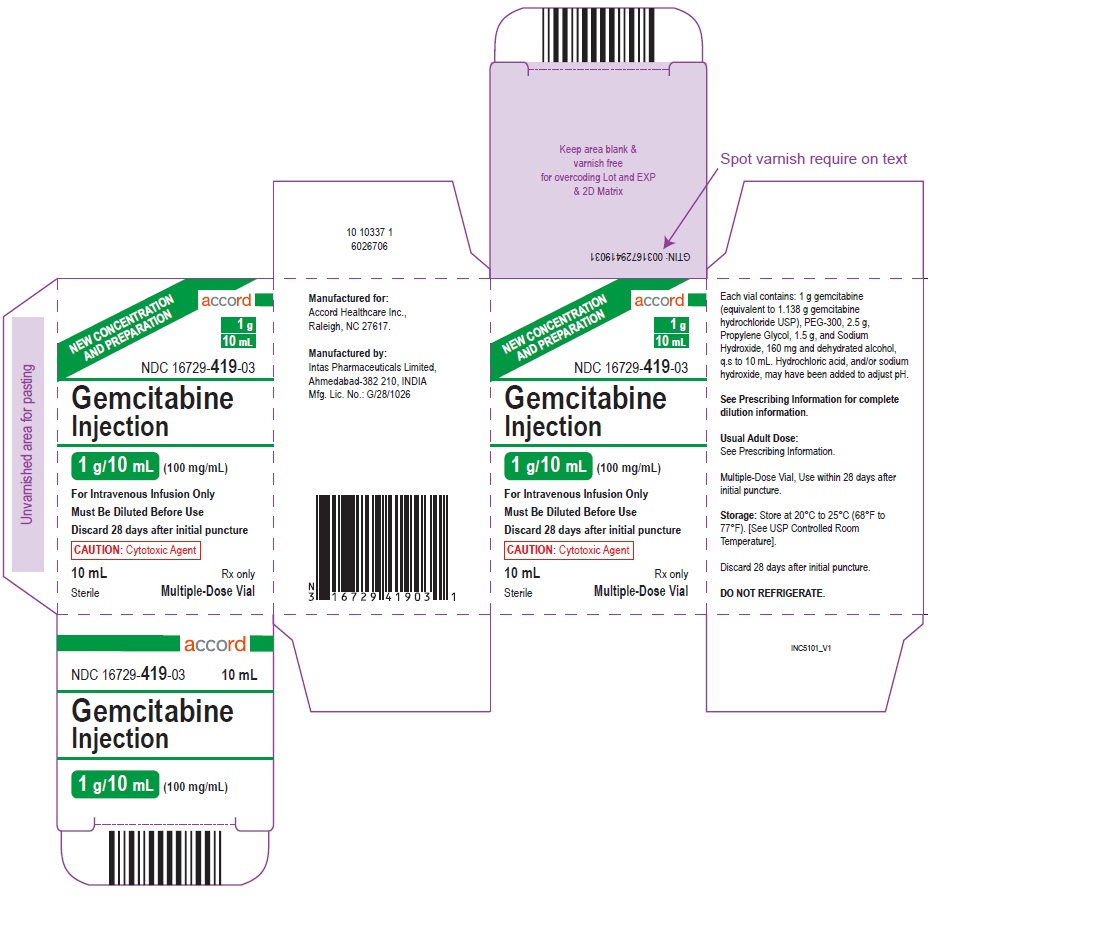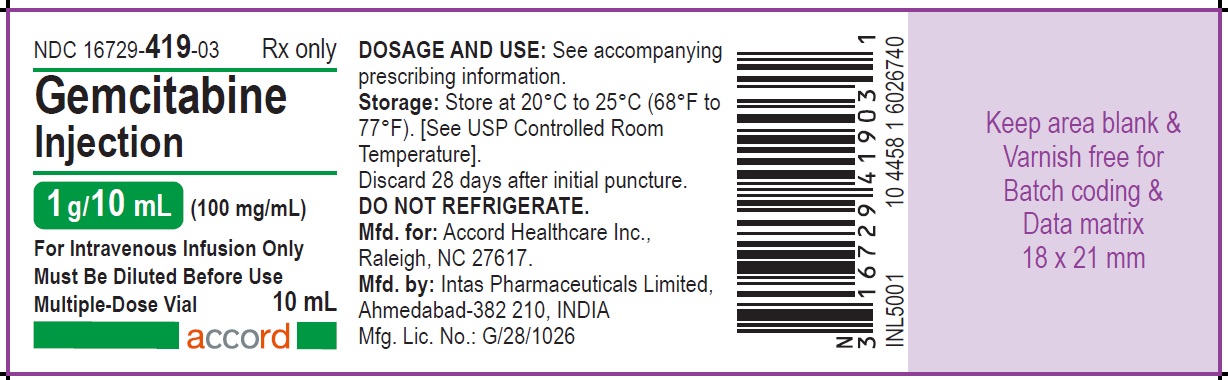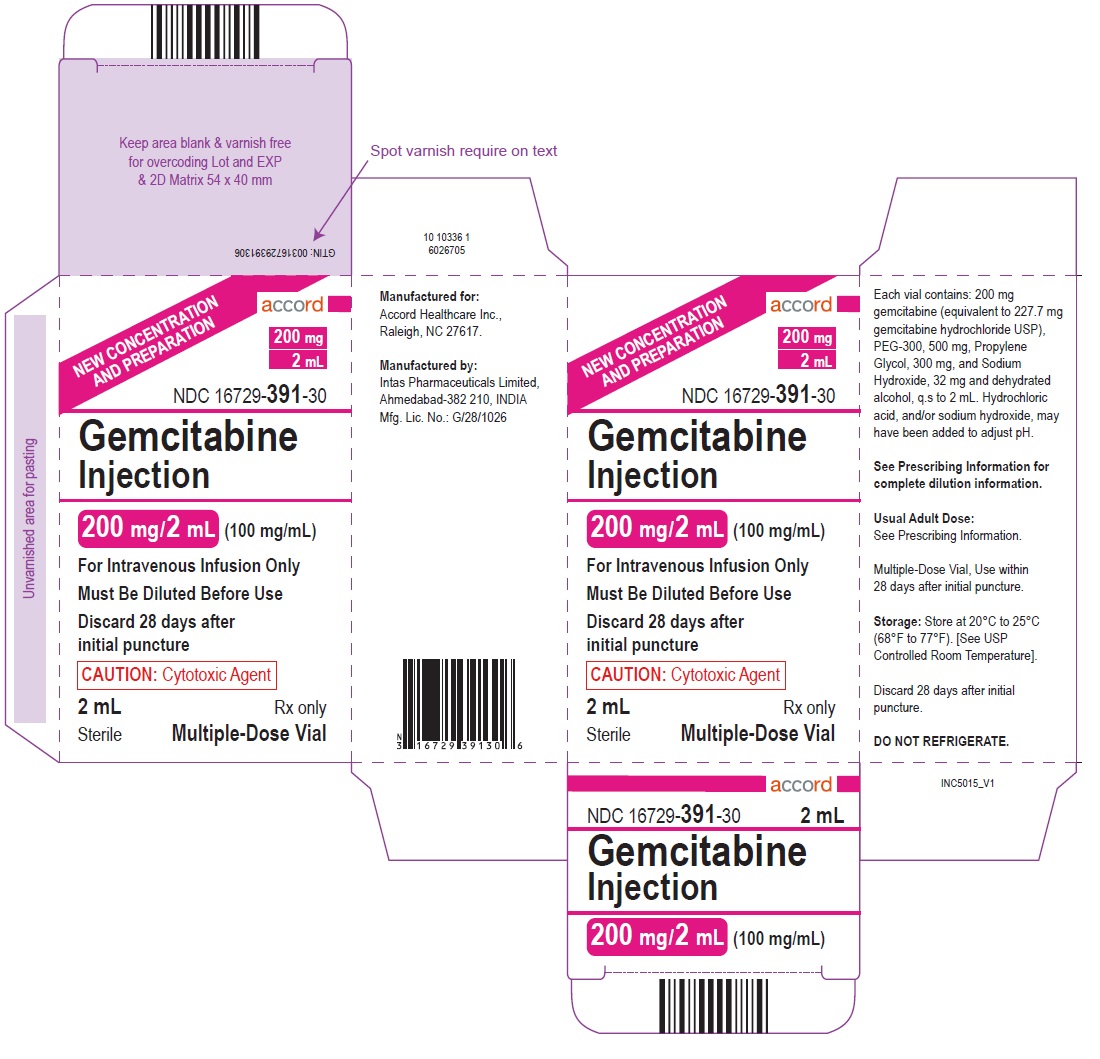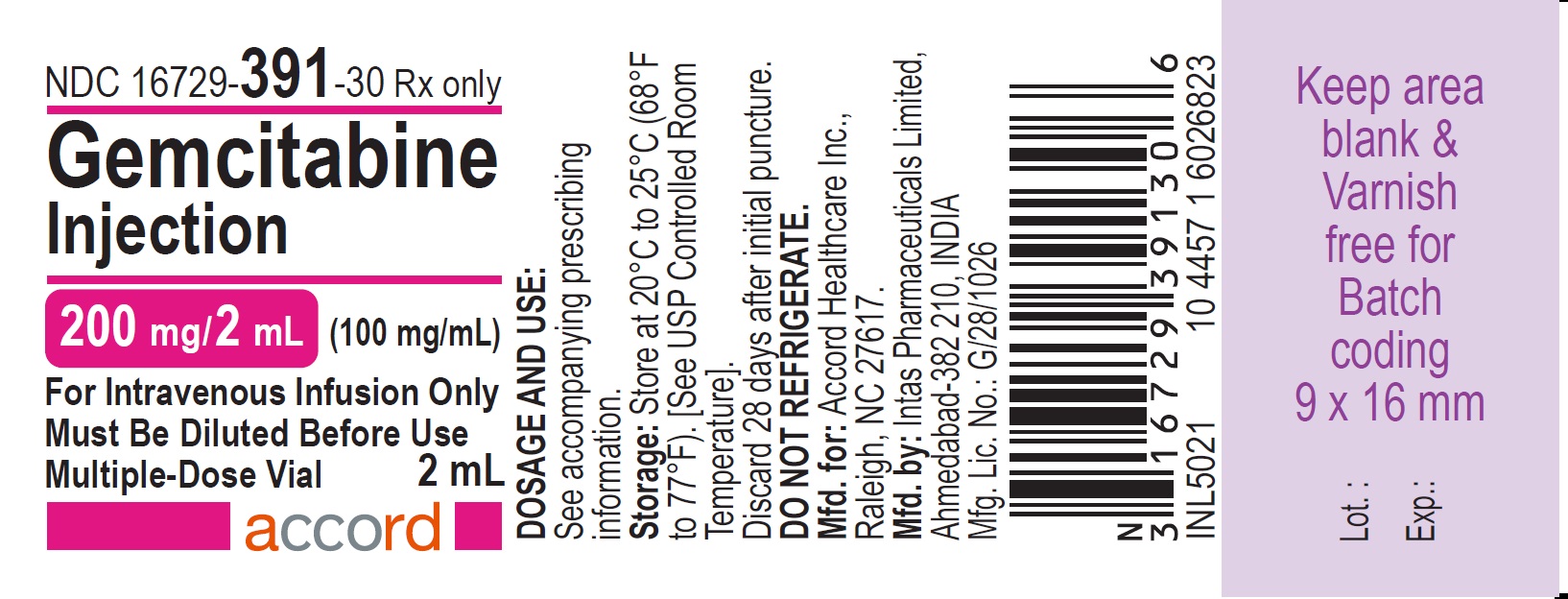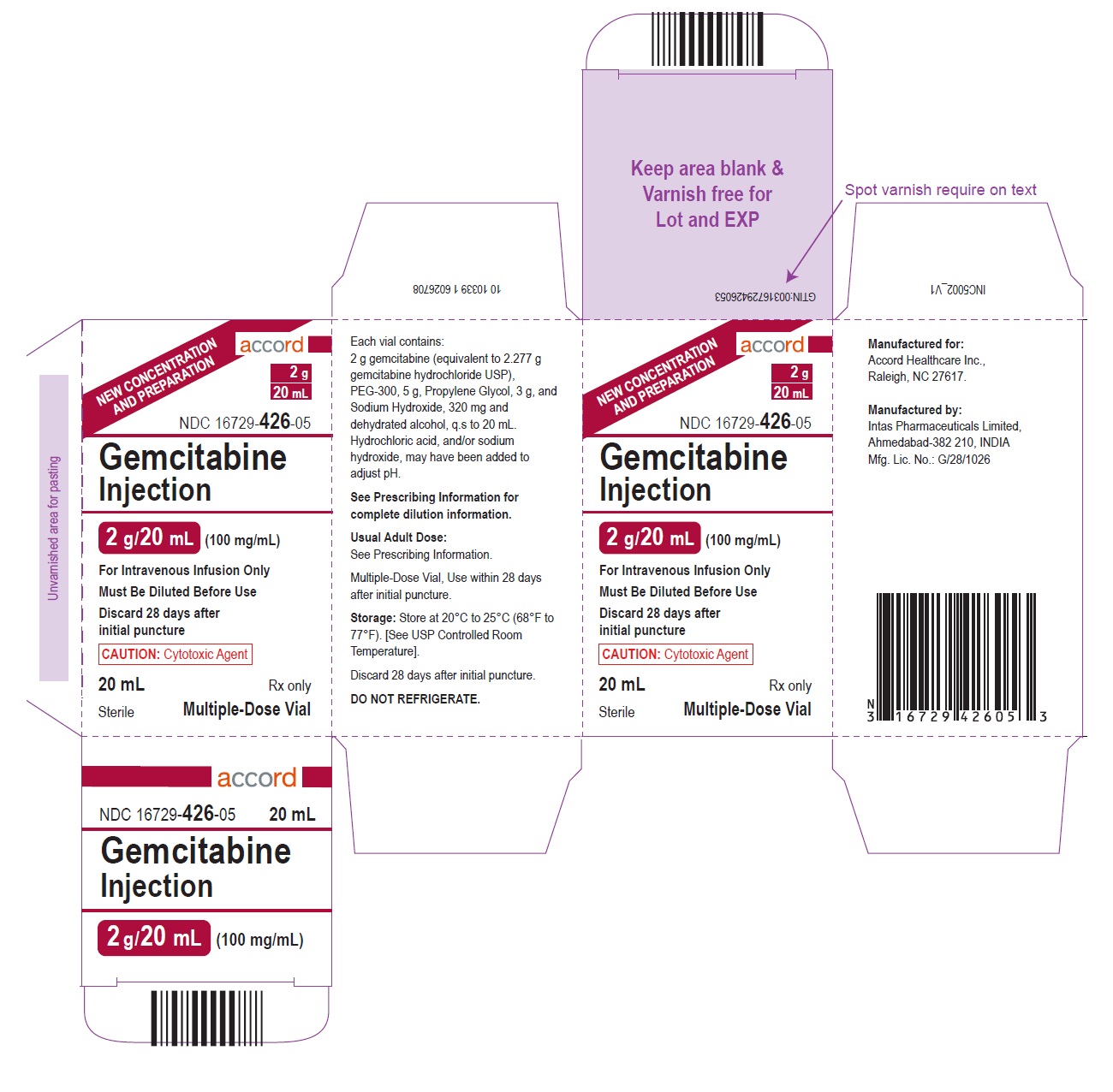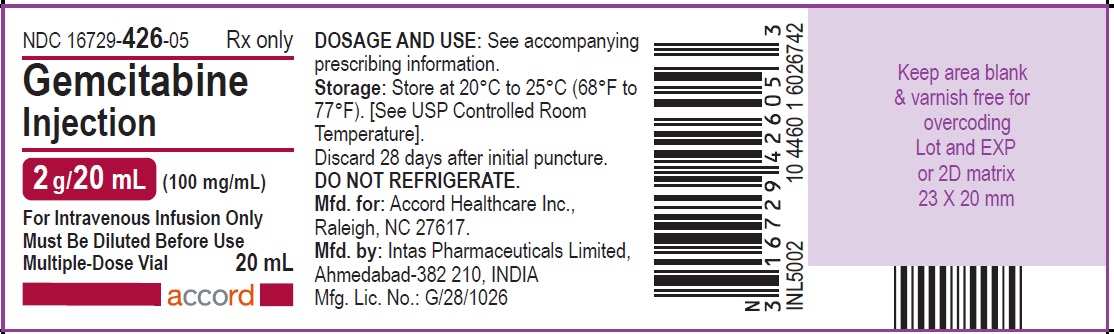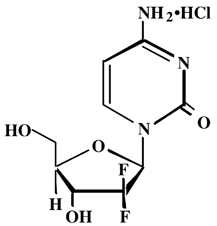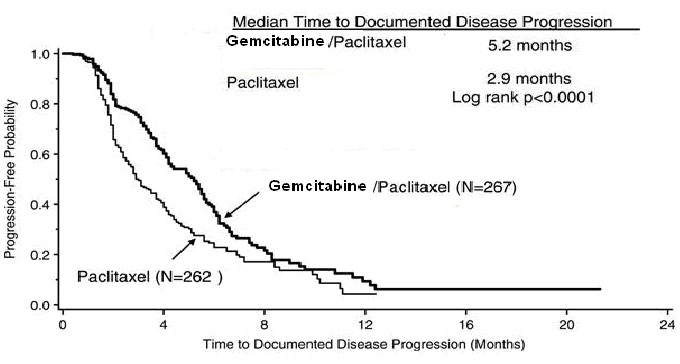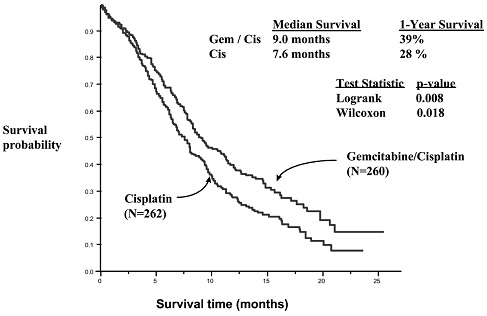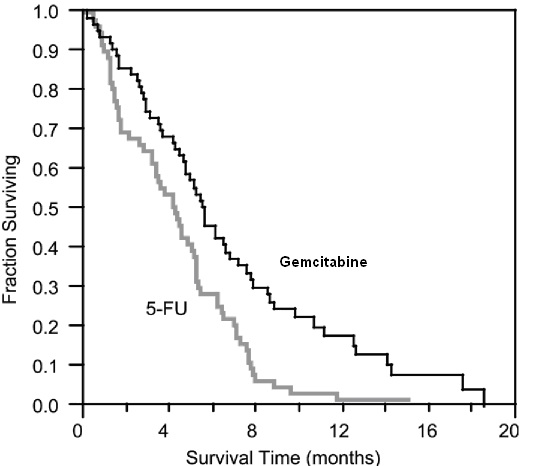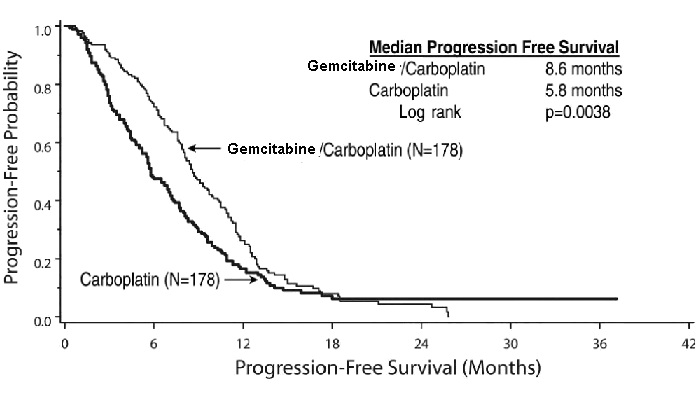 DRUG LABEL: GEMCITABINE
NDC: 16729-391 | Form: INJECTION, SOLUTION
Manufacturer: Accord Healthcare Inc.
Category: prescription | Type: HUMAN PRESCRIPTION DRUG LABEL
Date: 20240924

ACTIVE INGREDIENTS: GEMCITABINE HYDROCHLORIDE 100 mg/1 mL
INACTIVE INGREDIENTS: ALCOHOL; POLYETHYLENE GLYCOL 300 250 mg/1 mL; PROPYLENE GLYCOL 150 mg/1 mL; SODIUM HYDROXIDE 16 mg/1 mL; HYDROCHLORIC ACID

HIGHLIGHTS OF PRESCRIBING INFORMATION

These highlights do not include all the information needed to use GEMCITABINE INJECTION safely and effectively. See full prescribing information for GEMCITABINE INJECTION.
GEMCITABINE injection, for intravenous use
Initial U.S. Approval: 1996

RECENT MAJOR CHANGES

Warnings and Precautions
Severe Cutaneous Adverse Reactions (SCARs) (5.3) 9/2024

1 INDICATIONS AND USAGE

Gemcitabine Injection is a nucleoside metabolic inhibitor indicated:

- in combination with carboplatin, for the treatment of advanced ovarian cancer that has relapsed at least 6 months after completion of platinum-based therapy. (1.1)
- in combination with paclitaxel, for first-line treatment of metastatic breast cancer after failure of prior anthracycline-containing adjuvant chemotherapy, unless anthracyclines were clinically contraindicated. (1.2)
- in combination with cisplatin for the treatment of non-small cell lung cancer. (1.3)
- as a single agent for the treatment of pancreatic cancer. (1.4)

2 DOSAGE AND ADMINISTRATION

Gemcitabine Injection is for intravenous use only.

- Ovarian Cancer:1000 mg/m^2over 30 minutes on Days 1 and 8 of each 21-day cycle. (2.1)
- Breast Cancer:1250 mg/m^2over 30 minutes on Days 1 and 8 of each 21-day cycle. (2.2)
- Non-Small Cell Lung Cancer:1000 mg/m^2over 30 minutes on Days 1, 8, and 15 of each 28-day cycle or 1250 mg/m^2over 30 minutes on Days 1 and 8 of each 21-day cycle. (2.3)
- Pancreatic Cancer:1000 mg/m^2over 30 minutes once weekly for the first 7 weeks, then one week rest, then once weekly for 3 weeks of each 28-day cycle. (2.4)

3 DOSAGE FORMS AND STRENGTHS

Gemcitabine Injection in multiple dose vials containing:

- 200 mg/2 mL (100 mg/mL) (3)
- 1 g/10 mL (100 mg/mL) (3)
- 1.5 g/15 mL (100 mg/mL) (3)
- 2 g/20 mL (100 mg/mL) (3)

4 CONTRAINDICATIONS

Patients with a known hypersensitivity to gemcitabine. (4)

5 WARNINGS AND PRECAUTIONS

- Schedule-Dependent Toxicity:Increased toxicity with infusion time greater than 60 minutes or dosing more frequently than once weekly. (5.1)
- Myelosuppression:Monitor for myelosuppression prior to each cycle and reduce or withhold dose for severe myelosuppression. (5.2, 5.8)
- Severe Cutaneous Adverse Reactions (SCARs):Permanently discontinue Gemcitabine for Injection if SCARs occur. (5.3)
- Pulmonary Toxicity and Respiratory Failure:Discontinue Gemcitabine Injection for unexplained dyspnea or other evidence of severe pulmonary toxicity. (5.4)
- Hemolytic Uremic Syndrome (HUS):): Monitor renal function prior to initiation and during treatment. Discontinue Gemcitabine Injection for HUS or severe renal impairment. (5.5)
- Hepatic Toxicity:Monitor hepatic function prior to initiation and during treatment. Discontinue Gemcitabine Injection for severe hepatic toxicity. (5.6)
- Embryo-Fetal Toxicity:Can cause fetal harm. Advise females and males of reproductive potential to use effective contraception. (5.6, 8.1)
- Exacerbation of Radiation Therapy Toxicity:May cause severe and life-threatening toxicity when administered during or within 7 days of radiation therapy. (5.8)
- Capillary Leak Syndrome:Discontinue Gemcitabine Injection. (5.9)
- Posterior Reversible Encephalopathy Syndrome (PRES):Discontinue Gemcitabine Injection. (5.10)

6 ADVERSE REACTIONS

The most common adverse reactions for the single agent (≥20%) are nausea/vomiting, anemia, increased aspartate aminotransferase (AST), increased alanine aminotransferase (ALT), neutropenia, increased alkaline phosphatase, proteinuria, fever, hematuria, rash, thrombocytopenia, dyspnea, and edema. (6.1)

To report SUSPECTED ADVERSE REACTIONS, contact Accord Healthcare Inc. at 1-866-941-7875 or FDA at 1-800-FDA-1088 or www.fda.gov/medwatch

8 USE IN SPECIFIC POPULATIONS

Lactation: Advise not to breastfeed. (8.2)

FULL PRESCRIBING INFORMATION

1 INDICATIONS AND USAGE

1.1 Ovarian Cancer

Gemcitabine Injection in combination with carboplatin is indicated for the treatment of patients with advanced ovarian cancer that has relapsed at least 6 months after completion of platinum-based therapy.

1.2 Breast Cancer

Gemcitabine Injection in combination with paclitaxel is indicated for the first-line treatment of patients with metastatic breast cancer after failure of prior anthracycline-containing adjuvant chemotherapy, unless anthracyclines were clinically contraindicated.

1.3 Non-Small Cell Lung Cancer

Gemcitabine Injection in combination with cisplatin is indicated for the first-line treatment of patients with inoperable, locally advanced (Stage IIIA or IIIB) or metastatic (Stage IV) non-small cell lung cancer (NSCLC).

1.4 Pancreatic Cancer

Gemcitabine Injection is indicated as first-line treatment for patients with locally advanced (nonresectable Stage II or Stage III) or metastatic (Stage IV) adenocarcinoma of the pancreas. Gemcitabine Injection is indicated for patients previously treated with fluorouracil.

2 DOSAGE AND ADMINISTRATION

2.1 Ovarian Cancer

Recommended Dose and Schedule

The recommended dosage of Gemcitabine Injection is 1000 mg/m^2intravenously over 30 minutes on Days 1 and 8 of each 21-day cycle in combination with carboplatin AUC 4 administered intravenously on Day 1 after Gemcitabine Injection administration. Refer to carboplatin prescribing information for additional information.

Dosage Modifications

Recommended Gemcitabine Injection dosage modifications for myelosuppression are described in Table 1and 2 [see Warnings and Precautions (5.2)]. Refer to the recommended dosage modifications for non-hematologic adverse reactions [see Dosage and Administration (2.5)].

Table 1: Recommended Dosage Modifications for Gemcitabine Injection for Myelosuppression on Day of Treatment in Ovarian Cancer
Treatment Day | Absolute Neutrophil Count (x 10^6/L) |  | Platelet Count (x 10^6/L) | Dosage Modification
Day 1 | Greater than or equal to 1500 Less than 1500 | and or | Greater than or equal to 100,000 Less than 100,000 | None Delay Treatment Cycle
Day 8 | Greater than or equal to 1500 1000 to 1499 Less than 1000 | and or or | Greater than or equal to 100,000 75,000 to 99,999 Less than 75,000 | None 50% of full dose Hold

Table 2: Recommended Dosage Modifications for Gemcitabine Injection for Myelosuppression in Previous Cycle in Ovarian Cancer
Occurrence | Myelosuppression During Treatment Cycle | Dosage Modification
Initial Occurrence | - Absolute neutrophil count less than 500 x 10^6/L for more than 5 days or - Absolute neutrophil count less than 100 x 10^6/L for more than 3 days or - Febrile neutropenia or - Platelets less than 25,000x10^6/L or - Cycle delay for more than one week due to toxicity | Permanently reduce Gemcitabine Injection to 800 mg/m^2on Days 1 and 8
Subsequent Occurrence | If any of the above toxicities occur after the initial dose reduction | Permanently reduce Gemcitabine Injection to 800 mg/m^2on Day 1 only

2.2 Breast Cancer

Recommended Dose and Schedule

The recommended dosage of Gemcitabine Injection is 1250 mg/m^2m2 intravenously over 30 minutes on Days 1 and 8 of each 21-day cycle in combination with paclitaxel 175 mg/m^2administered as a 3-hour intravenous infusion on Day 1 before Gemcitabine Injection administration. Refer to paclitaxel prescribing information for additional information.

Dosage Modifications

Recommended Gemcitabine Injection dosage modifications for myelosuppression are described in Table 3 [see Warnings and Precautions (5.2)]. Refer to the recommended dosage modifications for non-hematologic adverse reactions [see Dosage and Administration (2.5)].

Table 3: Recommended Dosage Modifications for Gemcitabine Injection for Myelosuppression on Day of Treatment in Breast Cancer
Treatment Day | Absolute Neutrophil Count (x 10^6/L) |  | Platelet Count (x 10^6/L) | Dosage Modification
Day 1 | Greater than or equal to 1500 | and | Greater than or equal to 100,000 | None
 | Less than 1500 | or | Less than 100,000 | Hold
Day 8 | Greater than or equal to 1200 | and | Greater than 75,000 | None
 | 1000 to 1199 | or | 50,000 to 75,000 | 75% of full dose
 | 700 to 999 | and | Greater than or equal to 50,000 | 50% of full dose
 | Less than 700 | or | Less than 50,000 | Hold

2.3 Non-Small Cell Lung Cancer

Recommended Dose and Schedule

28-day schedule

The recommended dosage of Gemcitabine Injection is 1000 mg/m^2m2 intravenously over 30 minutes on Days 1, 8, and 15 of each 28-day cycle in combination with cisplatin 100 mg/m^2administered intravenously on Day 1 after Gemcitabine Injection administration.

21-day schedule

The recommended dosage of Gemcitabine Injection is 1250 mg/m^2intravenously over 30 minutes on Days 1 and 8 of each 21-day cycle in combination with cisplatin 100 mg/m^2administered intravenously on Day 1 after Gemcitabine Injection administration.

Refer to cisplatin prescribing information for additional information.

Dosage Modifications

Recommended dosage modifications for Gemcitabine Injection myelosuppression are described in Table 4 [see Warnings and Precautions (5.2)]. Refer to the recommended dosage modifications for non-hematologic adverse reactions [see Dosage and Administration (2.5)].

2.4 Pancreatic Cancer

Recommended Dose and Schedule

The recommended dosage of Gemcitabine Injection is 1000 mg/m^2intravenously over 30 minutes. The recommended treatment schedule is as follows:

- Weeks 1 to 8: weekly dosing for the first 7 weeks followed by one week rest.
- After week 8: weekly dosing on Days 1, 8, and 15 of each 28-day cycle.

Dosage Modifications

Recommended dosage modifications for Gemcitabine Injection for myelosuppression are described in Table 4 [see Warnings and Precautions (5.2)]. Refer to the recommended dosage modifications for non-hematologic adverse reactions [see Dosage and Administration (2.5)].

Table 4: Recommended Dosage Modifications for Gemcitabine Injection for Myelosuppression in Pancreatic Cancer and Non-Small Cell Lung Cancer
Absolute Neutrophil Count (x10^6/L) |  | Platelet Count (x10^6/L) | Dosage Modification
Greater than or equal to 1000 | and | Greater than or equal to 100,000 | None
500 to 999 | or | 50,000 to 99,999 | 75% of full dose
Less than 500 | or | Less than 50,000 | Hold

2.5 Dosage Modifications for Non-Hematologic Adverse Reactions

Permanently discontinue Gemcitabine Injection for any of the following:

- Severe Cutaneous Adverse Reactions (SCARs) [see Warnings and Precautions (5.3)]
- Unexplained dyspnea or evidence of severe pulmonary toxicity [see Warnings and Precautions (5.4)]
- Hemolytic uremic syndrome (HUS) or severe renal impairment [see Warnings and Precautions (5.5)]
- Severe hepatic toxicity [see Warnings and Precautions (5.6)]
- Capillary leak syndrome (CLS) [see Warnings and Precautions (5.9)]
- Posterior reversible encephalopathy syndrome (PRES) [see Warnings and Precautions (5.10)]

Withhold Gemcitabine Injection or reduce dose by 50% for other Grade 3 or 4 non-hematological adverse reactions until resolved. No dose modifications are recommended for alopecia, nausea, or vomiting.

2.6 Preparation and Administration

Gemcitabine Injection is a cytotoxic drug. Follow applicable special handling and disposal procedures.^1

Exercise caution and wear gloves when preparing Gemcitabine Injection solutions. Immediately wash the skin thoroughly or rinse the mucosa with copious amounts of water if Gemcitabine Injection contacts the skin or mucus membranes. Death has occurred in animal studies due to dermal absorption.

Preparation

- Inspect solution and discard vial if particulate matter or discoloration is observed.
- Dilute Gemcitabine Injection with 0.9% Sodium Chloride Injection to a minimum final concentration of at least 0.1 mg/mL.
- Mix diluted solution by gentle inversion. Do not shake.

After dilution with 0.9% Sodium Chloride Injection, inspect the diluted Gemcitabine Injection solution visually for particulate matter and discoloration. Discard if particulate matter or discoloration is found.

Storage

- After initial withdrawal with a needle, use the remaining portion in the vial or discard within 28 days.
- Store diluted Gemcitabine Injection solution at controlled room temperature 20°C to 25°C (68°F to 77°F). Discard the diluted solution after 24 hours.

Administration

- Inspect the diluted solution for particulate matter and discoloration prior to administration. Do not administer if particulate matter or discoloration is found.

The compatibility of Gemcitabine Injection with other drugs has not been studied.

No incompatibilities have been observed with infusion bottles or polyvinyl chloride bags and administration sets.

3 DOSAGE FORMS AND STRENGTHS

Injection: 100 mg/mL of gemcitabine as a clear, colorless to pale yellow solution in sterile multiple-dose vials:

- 200 mg/2 mL (100 mg/mL)
- 1 g/10 mL (100 mg/mL)
- 1.5 g/15 mL (100 mg/mL)
- 2 g/20 mL (100 mg/mL)

4 CONTRAINDICATIONS

Gemcitabine Injection is contraindicated in patients with a known hypersensitivity to gemcitabine. Reactions include anaphylaxis [see Adverse Reactions (6.1)].

5 WARNINGS AND PRECAUTIONS

5.1 Schedule-Dependent Toxicity

In clinical trials evaluating the maximum tolerated dose of gemcitabine, prolongation of the infusion time beyond 60 minutes or more frequent than weekly dosing resulted in an increased incidence of clinically significant hypotension, severe flu-like symptoms, myelosuppression, and asthenia. The half-life of gemcitabine is influenced by the length of the infusion [see Clinical Pharmacology (12.3)] . Refer to the recommended Gemcitabine Injection dosage [see Dosage and Administration (2.1, 2.2, 2.3, 2.4)].

5.2 Myelosuppression

Myelosuppression manifested by neutropenia, thrombocytopenia, and anemia occurs with gemcitabine as a single agent and the risks are increased when gemcitabine is combined with other cytotoxic drugs. In clinical trials, Grade 3-4 neutropenia, anemia, and thrombocytopenia occurred in 25%, 8%, and 5%, respectively of the 979 patients who received single agent gemcitabine. The frequencies of Grade 3-4 neutropenia, anemia, and thrombocytopenia varied from 48% to 71%, 8% to 28%, and 5% to 55%, respectively, in patients receiving gemcitabine in combination with another drug [see Adverse Reactions (6.1)] .

Prior to each dose of Gemcitabine Injection, obtain a complete blood count (CBC), with a differential and a platelet count. Modify the Gemcitabine Injection dosage as recommended [see Dosage and Administration (2.1, 2.2, 2.3, 2.4)] .

5.3 Severe Cutaneous Adverse Reactions (SCARs)

SCARs, including Stevens-Johnson syndrome (SJS), toxic epidermal necrolysis (TEN), drug reaction with eosinophilia and systemic symptoms (DRESS), and acute generalized exanthematous pustulosis (AGEP), which can be lifethreatening or fatal, have been reported in association with gemcitabine treatment [see Adverse Reactions (6.2)] . Monitor patients for signs and symptoms of severe cutaneous adverse reactions. Permanently discontinue gemcitabine in patients who develop SCARs.

5.4 Pulmonary Toxicity and Respiratory Failure

Pulmonary toxicity, including interstitial pneumonitis, pulmonary fibrosis, pulmonary edema, and adult respiratory distress syndrome (ARDS), has been reported. In some cases, these pulmonary events can lead to fatal respiratory failure despite the discontinuation of therapy. The onset of pulmonary symptoms may occur up to 2 weeks after the last dose of gemcitabine [see Adverse Reactions (6.1, 6.2)] .

Permanently discontinue Gemcitabine Injection in patients who develop unexplained dyspnea, with or without bronchospasm, or evidence of severe pulmonary toxicity.

5.5 Hemolytic Uremic Syndrome

Hemolytic uremic syndrome (HUS), including fatalities from renal failure or the requirement for dialysis, can occur with gemcitabine. In clinical trials, HUS occurred in 0.25% of 2429 patients. Most fatal cases of renal failure were due to HUS [see Adverse Reactions (6.1)] . Serious cases of thrombotic microangiopathy (TMA) other than HUS have been reported with gemcitabine [see Adverse Reactions (6.2)] .

Assess renal function prior to initiation of Gemcitabine Injection and periodically during treatment. Consider the diagnosis of HUS in patients who develop anemia with evidence of microangiopathic hemolysis; increased bilirubin or LDH; reticulocytosis; severe thrombocytopenia; or renal failure (increased serum creatinine or BUN). Permanently discontinue Gemcitabine Injection in patients with HUS or severe renal impairment. Renal failure may not be reversible even with the discontinuation of therapy.

5.6 Hepatic Toxicity

Drug-induced liver injury, including liver failure and death, has been reported in patients receiving gemcitabine alone or with other potentially hepatotoxic drugs [see Adverse Reactions (6.1, 6.2)] . Administration of gemcitabine in patients with concurrent liver metastases or a pre-existing medical history of hepatitis, alcoholism, or liver cirrhosis can lead to exacerbation of the underlying hepatic insufficiency.

Assess hepatic function prior to initiation of Gemcitabine Injection and periodically during treatment. Permanently discontinue Gemcitabine Injection in patients who develop severe hepatic toxicity.

5.7 Embryo-Fetal Toxicity

Based on animal data and its mechanism of action, Gemcitabine Injection can cause fetal harm when administered to a pregnant woman. Gemcitabine was teratogenic, embryotoxic, and fetotoxic in mice and rabbits.

Advise pregnant women of the potential risk to a fetus. Advise females of reproductive potential to use effective contraception during treatment with Gemcitabine Injection and for 6 months after the final dose. Advise male patients with female partners of reproductive potential to use effective contraception during treatment with Gemcitabine Injection and for 3 months following the final dose [see Use in Specific Populations (8.1, 8.3)] .

5.8 Exacerbation of Radiation Therapy Toxicity

Gemcitabine is not recommended for use in combination with radiation therapy.

Concurrent (given together or ≤7 days apart)

Life-threatening mucositis, especially esophagitis and pneumonitis occurred in a trial in which gemcitabine was administered at a dose of 1000 mg/m^2to patients with non-small cell lung cancer for up to 6 consecutive weeks concurrently with thoracic radiation.

Non-concurrent (given >7 days apart)

Excessive toxicity has not been observed when gemcitabine is administered more than 7 days before or after radiation. Radiation recall has been reported in patients who received gemcitabine after prior radiation.

5.9 Capillary Leak Syndrome

Capillary leak syndrome (CLS) with severe consequences has been reported in patients receiving gemcitabine as a single agent or in combination with other chemotherapeutic agents [see Adverse Reactions (6.2)] . Permanently discontinue Gemcitabine Injection if CLS develops during therapy.

5.10 Posterior Reversible Encephalopathy Syndrome

Posterior reversible encephalopathy syndrome (PRES) has been reported in patients receiving gemcitabine as a single agent or in combination with other chemotherapeutic agents [see Adverse Reactions (6.2)] . PRES can present with headache, seizure, lethargy, hypertension, confusion, blindness, and other visual and neurologic disturbances. Confirm the diagnosis of PRES with magnetic resonance imaging (MRI). Permanently discontinue Gemcitabine Injection if PRES develops during therapy.

6 ADVERSE REACTIONS

The following clinically significant adverse reactions are described elsewhere in the labeling:

- Hypersensitivity [see Contraindications (4)]
- Schedule-Dependent Toxicity [see Warnings and Precautions (5.1)]
- Myelosuppression [see Warnings and Precautions (5.2)]
- Severe Cutaneous Adverse Reactions [see Warnings and Precautions (5.3)]
- Pulmonary Toxicity and Respiratory Failure [see Warnings and Precautions (5.4)]
- Hemolytic Uremic Syndrome [see Warnings and Precautions (5.5)]
- Hepatic Toxicity [see Warnings and Precautions (5.6)]
- Exacerbation of Radiation Therapy Toxicity [see Warnings and Precautions (5.8)]
- Capillary Leak Syndrome [see Warnings and Precautions (5.9)]
- Posterior Reversible Encephalopathy Syndrome [see Warnings and Precautions (5.10)]

6.1 Clinical Trials Experience

Because clinical trials are conducted under widely varying conditions, adverse reaction rates observed in the clinical trials of a drug cannot be directly compared to rates in the clinical trials of another drug and may not reflect the rates observed in practice.

Single Agent

The data described below reflect exposure to gemcitabine as a single agent administered at doses between 800 mg/m^2to 1250 mg/m^2intravenously over 30 minutes once weekly in 979 patients with various malignancies. The most common (≥20%) adverse reactions of single agent gemcitabine are nausea/vomiting, anemia, increased alanine aminotransferase (ALT), increased aspartate aminotransferase (AST), neutropenia, increased alkaline phosphatase, proteinuria, fever, hematuria, rash, thrombocytopenia, dyspnea, and edema. The most common (≥5%) Grade 3 or 4 adverse reactions were neutropenia, nausea/vomiting, increased ALT, increased alkaline phosphatase, anemia, increased AST, and thrombocytopenia. Approximately 10% of the 979 patients discontinued gemcitabine due to adverse reactions. Adverse reactions resulting in discontinuation of gemcitabine in 2% of 979 patients were cardiovascular adverse reactions (myocardial infarction, cerebrovascular accident, arrhythmia, and hypertension) and adverse reactions resulting in discontinuation of gemcitabine in < 1% of 979 patients were anemia, thrombocytopenia, hepatic dysfunction, renal dysfunction, nausea/vomiting, fever, rash, dyspnea, hemorrhage, infection, stomatitis, somnolence, flu-like syndrome, and edema.

Tables 5and 6present the incidence of selected adverse reactions and laboratory abnormalities reported in patients with various malignancies receiving single agent gemcitabine across 5 clinical trials. Additional clinically significant adverse reactions are provided following Table 6.

Table 5: Selected Adverse Reactions Occurring in ≥10% of Patients Receiving Single Agent Gemcitabinea
 | Gemcitabineb
Adverse Reactionsb | All Grades (%) | Grade 3 (%) | Grade 4 (%)
Nausea and Vomiting | 69 | 13 | 1
Fever | 41 | 2 | 0
Rash | 30 | <1 | 0
Dyspnea | 23 | 3 | <1
Diarrhea | 19 | 1 | 0
Hemorrhage | 17 | <1 | <1
Infection | 16 | 1 | <1
Alopecia | 15 | <1 | 0
Stomatitis | 11 | <1 | 0
Somnolence | 11 | <1 | <1
Paresthesias | 10 | <1 | 0
aGrade based on criteria from the World Health Organization (WHO).
bFor approximately 60% of patients, non-laboratory adverse reactions were graded only if assessed to be possibly drug-related.
cN=699-974; all patients with laboratory or non-laboratory data.

Table 6: Selected Laboratory Abnormalities Occurring in Patients Receiving Single Agent Gemcitabinea
 | Gemcitabinec
Laboratory Abnormalityb | All Grades (%) | Grade 3 (%) | Grade 4 (%)
Hematologic
Anemia | 68 | 7 | 1
Neutropenia | 63 | 19 | 6
Thrombocytopenia | 24 | 4 | 1
Hepatic
Increased ALT | 68 | 8 | 2
Increased AST | 67 | 6 | 2
Increased alkaline phosphatase | 55 | 7 | 2
Hyperbilirubinemia | 13 | 2 | <1
Renal
Proteinuria | 45 | <1 | 0
Hematuria | 35 | <1 | 0
Increased BUN | 16 | 0 | 0
Increased creatinine | 8 | <1 | 0
aGrade based on criteria from the WHO.
bRegardless of causality.
cN=699-974; all patients with laboratory or non-laboratory data

Additional adverse reactions include the following:

- Transfusion requirements: Red blood cell transfusions (19%); platelet transfusions (<1%)
- Edema: Edema (13%), peripheral edema (20%), generalized edema (<1%)
- Flu-like Symptoms: Fever, asthenia, anorexia, headache, cough, chills, myalgia, insomnia, rhinitis, sweating and/or malaise (19%)
- Infection: Sepsis (<1%)
- Extravasation: Injection-site reactions (4%)
- Allergic: Bronchospasm (<2%); anaphylactoid reactions

Ovarian Cancer

Tables 7and 8present the incidence of selected adverse reactions and laboratory abnormalities, occurring in ≥10% of gemcitabine-treated patients and at a higher incidence in the gemcitabine with carboplatin arm, reported in a randomized trial (Study 1) of gemcitabine with carboplatin (n=175) compared to carboplatin alone (n=174) for the second-line treatment of ovarian cancer in women with disease that had relapsed more than 6 months following first-line platinum-based chemotherapy [see Clinical Studies (14.1)] .

Additional clinically significant adverse reactions, occurring in <10% of patients, are provided following table 8.

The proportion of patients with dose adjustments for carboplatin (1.8% versus 3.8%), doses of carboplatin omitted (0.2% versus 0) and discontinuing treatment for adverse reactions (11% versus 10%), were similar between arms. Dose adjustment for gemcitabine occurred in 10% of patients and gemcitabine dose was omitted in 14% of patients in the gemcitabine/carboplatin arm.

Table 7: Adverse Reactions Occurring in >10% of Patients Receiving Gemcitabine with Carboplatin and at Higher Incidence than in Patients Receiving Single Agent Carboplatin [Between Arm Difference of ≥5% (All Grades) or ≥2% (Grades 3-4)] in Study 1a
Adverse Reactionsb | Gemcitabine/Carboplatin (N=175) |  |  | Carboplatin (N=174)
Adverse Reactionsb | All Grades (%) | Grade 3 (%) | Grade 4 (%) | All Grades (%) | Grade 3 (%) | Grade 4 (%)
Nausea | 69 | 6 | 0 | 61 | 3 | 0
Alopecia | 49 | 0 | 0 | 17 | 0 | 0
Vomiting | 46 | 6 | 0 | 36 | 2 | <1
Constipation | 42 | 6 | 1 | 37 | 3 | 0
Fatigue | 40 | 3 | <1 | 32 | 5 | 0
Diarrhea | 25 | 3 | 0 | 14 | <1 | 0
Stomatitis/pharyngitis | 22 | <1 | 0 | 13 | 0 | 0
aGrade based on National Cancer Institute CTC Version 2.0.
bRegardless of causality.

Table 8: Laboratory Abnormalities Occurring in Patients Receiving Gemcitabine with Carboplatin and at Higher Incidence than in Patients Receiving Single Agent Carboplatin [Between Arm Difference of ≥5% (All Grades) or ≥2% (Grades 3-4)] in Study 1a
Laboratory Abnormalityb | Gemcitabine/Carboplatin (N=175) |  |  | Carboplatin (N=174)
Laboratory Abnormalityb | All Grades (%) | Grade 3 (%) | Grade 4 (%) | All Grades (%) | Grade 3 (%) | Grade 4 (%)
Hematologic
Neutropenia | 90 | 42 | 29 | 58 | 11 | 1
Anemia | 86 | 22 | 6 | 75 | 9 | 2
Thrombocytopenia | 78 | 30 | 5 | 57 | 10 | 1
RBC Transfusionsc | 38 | - | - | 15 | - | -
Platelet Transfusionsc | 9 | - | - | 3 | - | -
aGrade based on National Cancer Institute CTC Version 2.0.
bRegardless of causality.
cPercent of patients receiving a transfusion. Transfusions are not CTC-graded events. Blood transfusions included both packed red blood cells and whole blood.

Hematopoietic growth factors were administered more frequently in the gemcitabine-containing arm: leukocyte growth factor (24% and 10%) and erythropoiesis-stimulating agent (7% and 3.9%).

The following clinically relevant, Grade 3 and 4 adverse reactions occurred more frequently in the gemcitabine with carboplatin arm: dyspnea (3.4% versus 2.9%), febrile neutropenia (1.1% versus 0), hemorrhagic event (2.3% versus 1.1 %), motor neuropathy (1.1% versus 0.6%), and rash/desquamation (0.6% versus 0).

Breast Cancer

Tables 9and 10present the incidence of selected adverse reactions and laboratory abnormalities, occurring in ≥10% of gemcitabine treated patients and at a higher incidence in the gemcitabine with paclitaxel arm, reported in a randomized trial (Study 2) of gemcitabine with paclitaxel (n=262) compared to paclitaxel alone (n=259) for the first-line treatment of metastatic breast cancer (MBC) in women who received anthracycline-containing chemotherapy in the adjuvant/neo-adjuvant setting or for whom anthracyclines were contraindicated [see Clinical Studies (14.2)] . Additional clinically significant adverse reactions, occurring in <10% of patients, are provided following Table 10.

The requirement for dose reduction of paclitaxel were higher for patients in the gemcitabine/paclitaxel arm (5% versus 2%). The number of paclitaxel doses omitted (<1%), the proportion of patients discontinuing treatment for adverse reactions (7% versus 5%) and the number of treatment-related deaths (1 patient in each arm) were similar between the two arms.

Table 9: Selected Adverse Reactions Occurring in Patients Receiving Gemcitabine with Paclitaxel and at Higher Incidence than in Patients Receiving Single Agent Paclitaxel [Between Arm Difference of ≥5% (All Grades) or ≥2% (Grades 3-4)] in Study 2a
Adverse Reactionsb | Gemcitabine/Paclitaxel (N=262) |  |  | Paclitaxel (N=259)
Adverse Reactionsb | All Grades (%) | Grade 3 (%) | Grade 4 (%) | All Grades (%) | Grade 3 (%) | Grade 4 (%)
Alopecia | 90 | 14 | 4 | 92 | 19 | 3
Neuropathy–Sensory | 64 | 5 | <1 | 58 | 3 | 0
Nausea | 50 | 1 | 0 | 31 | 2 | 0
Fatigue | 40 | 6 | <1 | 28 | 1 | <1
Vomiting | 29 | 2 | 0 | 15 | 2 | 0
Diarrhea | 20 | 3 | 0 | 13 | 2 | 0
Anorexia | 17 | 0 | 0 | 12 | <1 | 0
Neuropathy–Motor | 15 | 2 | <1 | 10 | <1 | 0
Stomatitis/Pharyngitis | 13 | 1 | <1 | 8 | <1 | 0
Fever | 13 | <1 | 0 | 3 | 0 | 0
Rash/Desquamation | 11 | <1 | <1 | 5 | 0 | 0
Febrile Neutropenia | 6 | 5 | <1 | 2 | 1 | 0
aGrade based on National Cancer Institute CTC Version 2.0.
bNon-laboratory events were graded only if assessed to be possibly drug-related

Table 10: Selected Laboratory Abnormalities Occurring in >10% of Patients Receiving Gemcitabine with Paclitaxel and at a Higher Incidence than Patients Receiving Single Agent Paclitaxel [Between Arm Difference of ≥5% (All Grades) or ≥2% (Grades 3-4)] in Study 2a
Laboratory Abnormalityb | Gemcitabine/Paclitaxel (N=262) |  |  | Paclitaxel (N=259)
Laboratory Abnormalityb | All Grades (%) | Grade 3 (%) | Grade 4 (%) | All Grades (%) | Grade 3 (%) | Grade 4 (%)
Hematologic
Anemia | 69 | 6 | 1 | 51 | 3 | <1
Neutropenia | 69 | 31 | 17 | 31 | 4 | 7
Thrombocytopenia | 26 | 5 | <1 | 7 | <1 | <1
Hepatobiliary
Increased ALT | 18 | 5 | <1 | 6 | <1 | 0
Increased AST | 16 | 2 | 0 | 5 | <1 | 0
aGrade based on National Cancer Institute CTC Version 2.0.
bRegardless of causality.

Clinically relevant Grade 3 or 4 dyspnea occurred with a higher incidence in the gemcitabine with paclitaxel arm compared with the paclitaxel arm (1.9% versus 0).

Non-Small Cell Lung Cancer

Tables 11and 12present the incidence of selected adverse reactions and laboratory abnormalities occurring in ≥10% of gemcitabine-treated patients and at a higher incidence in the gemcitabine with cisplatin arm, reported in a randomized trial (Study 3) of gemcitabine with cisplatin (n=260) administered in 28-day cycles as compared to cisplatin alone (n=262) in patients receiving first-line treatment for locally advanced or metastatic NSCLC [see Clinical Studies (14.3)] .

Patients randomized to gemcitabine with cisplatin received a median of 4 cycles of treatment and those randomized to cisplatin alone received a median of 2 cycles of treatment. In this trial, the requirement for dose adjustments (>90% versus 16%), discontinuation of treatment for adverse reactions (15% versus 8%), and the proportion of patients hospitalized (36% versus 23%) were all higher for patients receiving gemcitabine with cisplatin compared to those receiving cisplatin alone. The incidence of febrile neutropenia (3% versus <1%), sepsis (4% versus 1%), Grade 3 cardiac dysrhythmias (3% versus <1%) were all higher in the gemcitabine with cisplatin arm compared to the cisplatin alone arm. The two-drug combination was more myelosuppressive with 4 (1.5%) possibly treatment-related deaths, including 3 resulting from myelosuppression with infection and one case of renal failure associated with pancytopenia and infection. No deaths due to treatment were reported on the cisplatin arm.

Table 11: Selected Adverse Reactions Occurring in ≥10% of Patients Receiving Gemcitabine with Cisplatin and at Higher Incidence than in Patients Receiving Single Agent Cisplatin [Between Arm Difference of ≥5% (All Grades) or ≥2% (Grades 3-4)] in Study 3a
Adverse Reactionsb | Gemcitabine/Cisplatinc |  |  | Cisplatind
Adverse Reactionsb | All Grades (%) | Grade 3 (%) | Grade 4 (%) | All Grades (%) | Grade 3 (%) | Grade 4 (%)
Nausea | 93 | 25 | 2 | 87 | 20 | <1
Vomiting | 78 | 11 | 12 | 71 | 10 | 9
Alopecia | 53 | 1 | 0 | 33 | 0 | 0
Neuro Motor | 35 | 12 | 0 | 15 | 3 | 0
Diarrhea | 24 | 2 | 2 | 13 | 0 | 0
Neuro Sensory | 23 | 1 | 0 | 18 | 1 | 0
Infection | 18 | 3 | 2 | 12 | 1 | 0
Fever | 16 | 0 | 0 | 5 | 0 | 0
Neuro Cortical | 16 | 3 | 1 | 9 | 1 | 0
Neuro Mood | 16 | 1 | 0 | 10 | 1 | 0
Local | 15 | 0 | 0 | 6 | 0 | 0
Neuro Headache | 14 | 0 | 0 | 7 | 0 | 0
Stomatitis | 14 | 1 | 0 | 5 | 0 | 0
Hemorrhage | 14 | 1 | 0 | 4 | 0 | 0
Hypotension | 12 | 1 | 0 | 7 | 1 | 0
Rash | 11 | 0 | 0 | 3 | 0 | 0
aGrade based on National Cancer Institute Common Toxicity Criteria (CTC).
bNon-laboratory events were graded only if assessed to be possibly drug-related.
cN=217-253; all gemcitabine/cisplatin patients with laboratory or non-laboratory data
dN=213-248; all cisplatin patients with laboratory or non-laboratory data

Table 12: Selected Laboratory Abnormalities Occurring in >10% of Patients Receiving Gemcitabine with Cisplatin and at Higher Incidence than in Patients Receiving Single Agent Cisplatin [Between Arm Difference of ≥5% (All Grades) or ≥2% (Grades 3-4)] in Study 3a
Laboratory Abnormalityb | Gemcitabine/Cisplatinc |  |  | Cisplatind
Laboratory Abnormalityb | All Grades (%) | Grade 3 (%) | Grade 4 (%) | All Grades (%) | Grade 3 (%) | Grade 4 (%)
Hematologic
Anemia | 89 | 22 | 3 | 67 | 6 | 1
Thrombocytopenia | 85 | 25 | 25 | 13 | 3 | 1
Neutropenia | 79 | 22 | 35 | 20 | 3 | 1
Lymphopenia | 75 | 25 | 18 | 51 | 12 | 5
RBC Transfusione | 39 | - | - | 13 | - | -
Platelet Transfusione | 21 | - | - | <1 | - | -
Renal
Increased Creatinine | 38 | 4 | <1 | 31 | 2 | <1
Proteinuria | 23 | 0 | 0 | 18 | 0 | 0
Hematuria | 15 | 0 | 0 | 13 | 0 | 0
Other Laboratory
Hyperglycemia | 30 | 4 | 0 | 23 | 3 | 0
Hypomagnesemia | 30 | 4 | 3 | 17 | 2 | 0
Hypocalcemia | 18 | 2 | 0 | 7 | 0 | <1
Hepatic
Increased Transaminases | 22 | 2 | 1 | 10 | 1 | 0
Increased Alkaline Phosphatase | 19 | 1 | 0 | 13 | 0 | 0
aGrade based on National Cancer Institute CTC.
bRegardless of causality.
cN=217-253; all gemcitabine/cisplatin patients with laboratory or non-laboratory data.
dN=213-248; all cisplatin patients with laboratory or non-laboratory data.
ePercent of patients receiving a transfusion. Percent transfusions are not CTC-graded events.

Tables 13and 14present the incidence of selected adverse reactions and laboratory abnormalities occurring in ≥10% of gemcitabine-treated patients and at a higher incidence in the gemcitabine with cisplatin arm, reported in a randomized trial (Study 4) of gemcitabine with cisplatin (n=69) administered in 21-day cycles as compared to etoposide with cisplatin (n=66) in patients receiving first-line treatment for locally advanced or metastatic NSCLC [see Clinical Studies (14.3)] . Additional clinically significant adverse reactions are provided following Table 14.

Patients in the gemcitabine/cisplatin (GC) arm received a median of 5 cycles and those in the etoposide/cisplatin (EC) arm received a median of 4 cycles. The majority of patients receiving more than one cycle of treatment required dose adjustments; 81% in the GC arm and 68% in the EC arm. The incidence of hospitalizations for adverse reactions was 22% in the GC arm and 27% in the EC arm. The proportion of patients who discontinued treatment for adverse reactions was higher in the GC arm (14% versus 8%). The proportion of patients who were hospitalized for febrile neutropenia was lower in the GC arm (7% versus 12%). There was one death attributed to treatment, a patient with febrile neutropenia and renal failure, which occurred in the GC arm.

Table 13: Selected Adverse Reactions in Patients Receiving Gemcitabine with Cisplatin in Study 4a
Adverse Reactionsb | Gemcitabine/Cisplatinc |  |  | Etoposide/Cisplatind
Adverse Reactionsb | All Grades (%) | Grade 3 (%) | Grade 4 (%) | All Grades (%) | Grade 3 (%) | Grade 4 (%)
Nausea and Vomiting | 96 | 35 | 4 | 86 | 19 | 7
Alopecia | 77 | 13 | 0 | 92 | 51 | 0
Paresthesias | 38 | 0 | 0 | 16 | 2 | 0
Infection | 28 | 3 | 1 | 21 | 8 | 0
Stomatitis | 20 | 4 | 0 | 18 | 2 | 0
Diarrhea | 14 | 1 | 1 | 13 | 0 | 2
Edemae | 12 | - | - | 2 | - | -
Rash | 10 | 0 | 0 | 3 | 0 | 0
Hemorrhage | 9 | 0 | 3 | 3 | 0 | 3
Fever | 6 | 0 | 0 | 3 | 0 | 0
Somnolence | 3 | 0 | 0 | 3 | 2 | 0
Flu-like Syndromee | 3 | - | - | 0 | - | -
Dyspnea | 1 | 0 | 1 | 3 | 0 | 0
aGrade based on criteria from the World Health Organization (WHO).
bNon-laboratory events were graded only if assessed to be possibly drug-related. .
cN=67-69; all gemcitabine/cisplatin patients with non-laboratory data.
dN=57-63; all cisplatin plus etoposide patients with non-laboratory data.
eFlu-like syndrome and edema were not graded.

Table 14: Selected Laboratory Abnormalities Occurring in Patients Receiving Gemcitabine with Cisplatin in Study 4a
Laboratory Abnormalitiesb | Gemcitabine /Cisplatinc |  |  | Etoposide /Cisplatind
Laboratory Abnormalitiesb | All Grades (%) | Grade 3 (%) | Grade 4 (%) | All Grades (%) | Grade 3 (%) | Grade 4 (%)
Hematologic
Anemia | 88 | 22 | 0 | 77 | 13 | 2
Neutropenia | 88 | 36 | 28 | 87 | 20 | 56
Thrombocytopenia | 81 | 39 | 16 | 45 | 8 | 5
Platelet Transfusione | 3 | - | - | 8 | - | -
RBC Transfusione | 29 | - | - | 21 | - | -
Hepatic
Increased Alkaline Phosphatase | 16 | 0 | 0 | 11 | 0 | 0
Increased ALT | 6 | 0 | 0 | 12 | 0 | 0
Increased AST | 3 | 0 | 0 | 11 | 0 | 0
Renal
Hematuria | 22 | 0 | 0 | 10 | 0 | 0
Proteinuria | 12 | 0 | 0 | 5 | 0 | 0
Increased BUN | 6 | 0 | 0 | 4 | 0 | 0
Increased Creatinine | 2 | 0 | 0 | 2 | 0 | 0
aGrade based on criteria from the WHO.
bRegardless of causality.
cN=67-69; all gemcitabine/cisplatin patients with laboratory or non-laboratory data.
dN=57-63; all etoposide/cisplatin patients with laboratory or non-laboratory data.
eWHO grading scale not applicable to proportion of patients with transfusions.

6.2 Postmarketing Experience

The following adverse reactions have been identified during postapproval use of gemcitabine. Because these reactions are reported voluntarily from a population of uncertain size, it is not always possible to reliably estimate their frequency or establish a causal relationship to drug exposure.

Blood and Lymphatic System:TMA

Cardiovascular:Congestive heart failure, myocardial infarction, arrhythmias, supraventricular arrhythmias

Vascular:Peripheral vasculitis, gangrene, capillary leak syndrome

Skin:Cellulitis, pseudocellulitis, severe cutaneous adverse reactions (SCARs), including Stevens-Johnson syndrome (SJS), toxic epidermal necrolysis (TEN), drug reaction with eosinophilia and systemic symptoms (DRESS), and acute generalized exanthematous pustulosis (AGEP); desquamation and bullous skin eruptions

Hepatic:Hepatic failure, hepatic veno-occlusive disease

Pulmonary:Interstitial pneumonitis, pulmonary fibrosis, pulmonary edema, adult respiratory distress syndrome (ARDS), pulmonary eosinophilia

Nervous System:Posterior reversible encephalopathy syndrome (PRES)

8 USE IN SPECIFIC POPULATIONS

8.1 Pregnancy

Risk Summary

Based on animal data and its mechanism of action, Gemcitabine Injection can cause fetal harm when administered to a pregnant woman [see Clinical Pharmacology (12.1)] . There are no available data on the use of gemcitabine in pregnant women. In animal reproduction studies, gemcitabine was teratogenic, embryotoxic, and fetotoxic in mice and rabbits (see Data). Advise pregnant women of the potential risk to a fetus [see Use in Special Populations (8.3)] .

In the U.S. general population, the estimated background risk of major birth defects and miscarriages in clinically recognized pregnancies is 2-4% and 15-20% respectively.

Data

Animal Data

Gemcitabine is embryotoxic in mice. Daily dosing of gemcitabine to pregnant mice increased the incidence of fetal malformation (cleft palate, incomplete ossification) at doses of 1.5 mg/kg/day [approximately 0.005 times the 1000 mg/m^2clinical dose based on body surface area (BSA)]. Gemcitabine was embryotoxic and fetotoxic in rabbits. Daily dosing of gemcitabine to pregnant rabbits resulted in fetotoxicity (decreased fetal viability, reduced litter sizes, and developmental delays) and increased the incidence of fetal malformations (fused pulmonary artery, absence of gall bladder) at doses of 0.1 mg/kg/day (approximately 0.002 times the 1000 mg/m^2clinical dose based on BSA).

8.2 Lactation

Risk Summary

There is no information regarding the presence of gemcitabine or its metabolites in human milk, or their effects on the breastfed infant or on milk production. Due to the potential for serious adverse reactions in breastfed infants, advise women not to breastfeed during treatment with Gemcitabine Injection and for at least one week following the last dose.

8.3 Females and Males of Reproductive Potential

Pregnancy Testing

Verify pregnancy status in females of reproductive potential prior to initiating Gemcitabine Injection [see Use in Specific Populations (8.1)].

Contraception

Gemcitabine Injection can cause fetal harm when administered to a pregnant woman [see Use in Specific Populations (8.1)].

Females

Because of the potential for genotoxicity, advise females of reproductive potential to use effective contraception during treatment with Gemcitabine Injection and for 6 months after the final dose.

Males

Because of the potential for genotoxicity, advise males with female partners of reproductive potential to use effective contraception during treatment with Gemcitabine Injection and for 3 months after the final dose [see Nonclinical Toxicology (13.1)].

Infertility

Males

Based on animal studies, gemcitabine may impair fertility in males of reproductive potential [see Nonclinical Toxicology (13.1)]. It is not known whether these effects on fertility are reversible.

8.4 Pediatric Use

The safety and effectiveness of gemcitabine have not been established in pediatric patients.

The safety and pharmacokinetics of gemcitabine were evaluated in a trial in pediatric patients with refractory leukemia. The maximum tolerated dose was 10 mg/m^2/min for 360 minutes weekly for three weeks followed by a one-week rest period.

The safety and activity of gemcitabine were evaluated in a trial of pediatric patients with relapsed acute lymphoblastic leukemia (22 patients) and acute myelogenous leukemia (10 patients) at a dose of 10 mg/m2/min administered over 360 minutes weekly for three weeks followed by a one-week rest period. Patients with M1 or M2 bone marrow on Day 28 who did not experience unacceptable toxicity were eligible to receive a maximum of one additional four-week course. Toxicities observed included myelosuppression, febrile neutropenia, increased serum transaminases, nausea, and rash/desquamation. No meaningful clinical activity was observed in this trial.

8.5 Geriatric Use

In clinical studies which enrolled 979 patients with various malignancies who received single agent gemcitabine, no overall differences in safety were observed between patients aged 65 and older and younger patients, with the exception of a higher rate of Grade 3-4 thrombocytopenia in older patients as compared to younger patients.

In a randomized trial in women with ovarian cancer (Study 1), 175 women received gemcitabine with carboplatin, of which 29% were age 65 years or older. Similar effectiveness was observed between older and younger women There was significantly higher Grade 3-4 neutropenia in women 65 years of age or older [see Dosage and Administration (2.1)] .

Gemcitabine clearance is affected by age; however, there are no recommended dose adjustments based on patients’ age [see Clinical Pharmacology (12.3)] .

8.6 Gender

Gemcitabine clearance is decreased in females [see Clinical Pharmacology (12.3)] . In single agent studies of gemcitabine, women, especially older women, were more likely not to proceed to a subsequent cycle and to experience Grade 3-4 neutropenia and thrombocytopenia [see Dosage and Administration (2.1, 2.2, 2.3, 2.4)] .

10 OVERDOSAGE

There is no known antidote for overdoses of gemcitabine. Myelosuppression, paresthesias, and severe rash were the principal toxicities seen when a single dose as high as 5700 mg/m^2was administered by intravenous infusion over 30 minutes every 2 weeks to several patients in a dose-escalation study. In the event of suspected overdose, monitor with appropriate blood counts and provide supportive therapy, as necessary.

11 DESCRIPTION

Gemcitabine is a nucleoside metabolic inhibitor. Gemcitabine hydrochloride is 2’-deoxy-2’,2’-difluorocytidine monohydrochloride (β-isomer) with the following molecular structure:.

Gemcitabine hydrochloride is a white to off white crystalline powder. The empirical formula for gemcitabine hydrochloride is C9H11F2N3O4• HCl and the molecular weight is 299.66.

Gemcitabine hydrochloride is soluble in water, slightly soluble in methanol, and practically insoluble in ethanol and polar organic solvents.

Gemcitabine Injection is a sterile, clear colorless to pale yellow solution that is provided in 100 mg/mL multiple-dose vials for intravenous use only. Gemcitabine Injection is available in four presentations: 200 mg/2 mL, 1 g/10 mL, 1.5 g/15 mL or 2 g/20 mL. Each mL contains 100 mg of gemcitabine free base (equivalent to 113.85 mg of gemcitabine hydrochloride), 250 mg PEG-300, 150 mg propylene glycol, and 16 mg sodium hydroxide in dehydrated alcohol. Sodium hydroxide and/or hydrochloric acid may have been added for pH adjustment.

12 CLINICAL PHARMACOLOGY

12.1 Mechanism of Action

Gemcitabine kills cells undergoing DNA synthesis and blocks the progression of cells through the G1/S-phase boundary. Gemcitabine is metabolized by nucleoside kinases to diphosphate (dFdCDP) and triphosphate (dFdCTP) nucleosides. Gemcitabine diphosphate inhibits ribonucleotide reductase, an enzyme responsible for catalyzing the reactions that generate deoxynucleoside triphosphates for DNA synthesis, resulting in reductions in deoxynucleotide concentrations, including dCTP. Gemcitabine triphosphate competes with dCTP for incorporation into DNA. The reduction in the intracellular concentration of dCTP by the action of the diphosphate enhances the incorporation of gemcitabine triphosphate into DNA (self-potentiation). After the gemcitabine nucleotide is incorporated into DNA, only one additional nucleotide is added to the growing DNA strands, which eventually results in the initiation of apoptotic cell death.

12.3 Pharmacokinetics

The pharmacokinetics of gemcitabine were examined in 353 patients with various solid tumors. Pharmacokinetic parameters were derived using data from patients treated for varying durations of therapy given weekly with periodic rest weeks and using both short infusions (<70 minutes) and long infusions (70 to 285 minutes). The total gemcitabine dose varied from 500 mg/m^2to 3600 mg/m^2.

Distribution

The volume of distribution was increased with infusion length. Volume of distribution of gemcitabine was 50 L/m^2following infusions lasting <70 minutes. For long infusions, the volume of distribution rose to 370 L/m^2.

Gemcitabine pharmacokinetics are linear and are described by a 2-compartment model. Population pharmacokinetic analyses of combined single and multiple dose studies showed that the volume of distribution of gemcitabine was significantly influenced by duration of infusion and sex. Gemcitabine plasma protein binding is negligible.

Elimination

Metabolism

The active metabolite, gemcitabine triphosphate, can be extracted from peripheral blood mononuclear cells. The half-life of the terminal phase for gemcitabine triphosphate from mononuclear cells ranges from 1.7 to 19.4 hours.

Excretion

Gemcitabine disposition was studied in 5 patients who received a single 1000 mg/m2 of radiolabeled drug as a 30-minute infusion. Within one week, 92% to 98% of the dose was recovered, almost entirely in the urine. Gemcitabine (<10%) and the inactive uracil metabolite, 2’-deoxy-2’,2’-difluorouridine (dFdU) accounted for 99% of the excreted dose. The metabolite dFdU is also found in plasma.

Specific Populations

Geriatric Patients

Clearance of gemcitabine was affected by age. The lower clearance in geriatric patients results in higher concentrations of gemcitabine for any given dose. Differences in either clearance or volume of distribution based on patient characteristics or the duration of infusion result in changes in half-life and plasma concentrations. Table 15shows plasma clearance and half-life of gemcitabine following short infusions for typical patients by age and sex.

Table 15: Gemcitabine Clearance and Half-Life for the “Typical” Patient
Age | Clearance Men (L/hr/m^2) | Clearance in Women (L/hr/m^2) | Half-LifeaMen (min) | Half-LifeaWomen (min)
29 | 92.2 | 69.4 | 42 | 49
45 | 75.7 | 57.0 | 48 | 57
65 | 55.1 | 41.5 | 61 | 73
79 | 40.7 | 30.7 | 79 | 94
aHalf-life for patients receiving <70 minute infusion.

Gemcitabine half-life for short infusions ranged from 42 to 94 minutes and for long infusions varied from 245 to 638 minutes, depending on age and sex, reflecting a greatly increased volume of distribution with longer infusions.

Male and Female Patients

Females have lower clearance and longer half-lives than male patients as described in Table 15.

Patients with Renal Impairment

No clinical studies have been conducted with gemcitabine in patients with decreased renal function.

Patients with Hepatic Impairment

No clinical studies have been conducted with gemcitabine in patients with decreased hepatic function.

Drug Interaction Studies

When gemcitabine (1250 mg/m^2on Days 1 and 8) and cisplatin (75 mg/m^2on Day 1) were administered in patients with NSCLC, the clearance of gemcitabine on Day 1 was 128 L/hr/m^2and on Day 8 was 107 L/hr/m^2. Data from patients with NSCLC demonstrate that gemcitabine and carboplatin given in combination does not alter the pharmacokinetics of gemcitabine or carboplatin compared to administration of either single agent; however, due to wide confidence intervals and small sample size, interpatient variability may be observed.

Data from metastatic breast cancer patients shows that gemcitabine has little or no effect on the pharmacokinetics (clearance and half-life) of paclitaxel and paclitaxel has little or no effect on the pharmacokinetics of gemcitabine.

13 NONCLINICAL TOXICOLOGY

13.1 Carcinogenesis, Mutagenesis, Impairment of Fertility

Long-term animal studies to evaluate the carcinogenic potential of gemcitabine have not been conducted. Gemcitabine was mutagenic in an in vitro mouse lymphoma (L5178Y) assay and was clastogenic in an in vivo mouse micronucleus assay. Gemcitabine intraperitoneal doses of 0.5 mg/kg/day [about 1/700 the 1000 mg/m^2clinical dose based on body surface area (BSA)] in male mice resulted in moderate to severe hypospermatogenesis, decreased fertility, and decreased implantations. In female mice, fertility was not affected but maternal toxicities were observed at 1.5 mg/kg/day administered intravenously (about 1/200 the 1000 mg/m^2clinical dose based on BSA) and fetotoxicity or embryolethality was observed at 0.25 mg/kg/day administered intravenously (about 1/1300 the 1000 mg/m^2clinical dose based on BSA).

14 CLINICAL STUDIES

14.1 Ovarian Cancer

The efficacy of gemcitabine was evaluated in a randomized trial (Study 1) conducted in women with advanced ovarian cancer that had relapsed at least 6 months after first-line platinum-based therapy. Patients were randomized to receive either gemcitabine 1000 mg/m2 on Days 1 and 8 of each 21-day cycle with carboplatin AUC 4 on Day 1 after gemcitabine administration (n=178) or carboplatin AUC 5 on Day 1 of each 21-day cycle (n=178). The major efficacy outcome measure was progression-free survival (PFS).

A total of 356 patients were enrolled. Demographics and baseline characteristics are shown in Table 16.

Efficacy results are presented in Table 17and Figure 1. The addition of gemcitabine to carboplatin resulted in statistically significant improvements in PFS and overall response rate. Approximately 75% of patients in each arm received additional chemotherapy for disease progression; 13 of 120 patients in the carboplatin alone arm received gemcitabine for treatment of disease progression. There was no significant difference in overall survival between the treatment arms.

Table 16: Baseline Demographics and Clinical Characteristics for Study 1
 | Gemcitabine /Carboplatin (N=178) | Carboplatin (N=178)
Median age, years | 59 | 58
Range | 36 to 78 | 21 to 81
Baseline ECOG performance status 0-1a | 94% | 95%
Disease Status
Evaluable | 8% | 3%
Bidimensionally measurable | 92% | 96%
Platinum-free intervalb
6-12 months | 40% | 40%
>12 months | 59% | 60%
First-line therapy
Platinum-taxane combination | 70% | 71%
Platinum-non-taxane combination | 29% | 28%
Platinum monotherapy | 1% | 1%
a5 patients on gemcitabine with carboplatin arm and 4 patients on carboplatin arm had no baseline Eastern Cooperative Oncology Group (ECOG) performance status.
b2 patients on gemcitabine with carboplatin arm and 1 patient on carboplatin arm had platinum-free interval < 6 months.

Table 17: Efficacy Results in Study 1
Efficacy Parameter | Gemcitabine /Carboplatin (N=178) | Carboplatin (N=178)
Progression-free Survival
Median (95% CIa) months | 8.6 (8.0, 9.7) | 5.8 (5.2, 7.1)
Hazard Ratio (95% CI) | 0.72 (0.57, 0.90)
p-valueb | p=0.0038
Overall Survival
Median (95% CI) months | 18.0 (16.2, 20.3) | 17.3 (15.2, 19.3)
Hazard Ratio (95% CI) | 0.98 (0.78, 1.24)
p-valueb | p=0.8977
Overall Response Rate by investigator | 47.2% | 30.9%
p-valuec | p=0.0016
CRd | 14.6% | 6.2%
PR plus PRNMe | 32.6% | 24.7%
Overall Response Ratefby independent review | 46.3% | 35.6%
p-valuec | p=0.11
CRd | 9.1% | 4.0%
PR plus PRNMe | 37.2% | 31.7%
aCI=confidence interval.
bLog rank, unadjusted.
cChi square.
dCR=Complete response.
ePR plus PRNM=Partial response plus partial response, non-measurable disease.
fIndependently reviewed cohort - gemcitabine/carboplatin (n=121), carboplatin (n=101); independent reviewers unable to measure disease detected by sonography or physical exam.

Figure 1: Kaplan-Meier Curves for Progression Free Survival in Study 1.

14.2 Breast Cancer

The efficacy of gemcitabine was evaluated in a multinational, randomized, open-label trial (Study 2) conducted in women receiving initial treatment for metastatic breast cancer and who have received prior adjuvant/neoadjuvant anthracycline chemotherapy unless clinically contraindicated. Patients were randomized to receive either gemcitabine 1250 mg/m2 on Days 1 and 8 of each 21-day cycle with paclitaxel 175 mg/m^2administered on Day 1 before gemcitabine administration (n=267) or paclitaxel 175 mg/m2 on Day 1 of each 21-day cycle (n=262). The major efficacy outcome measure was time to documented disease progression.

A total of 529 patients were enrolled. Demographic and baseline characteristics were similar between treatment arms (Table 18).

Efficacy results are presented in Table 19and Figure 2. The addition of gemcitabine to paclitaxel resulted in statistically significant improvement in time to documented disease progression and overall response rate compared to paclitaxel alone. There was no significant difference in overall survival.

Table 18: Baseline Demographics and Clinical Characteristics for Study 2
 | Gemcitabine/Paclitaxel (N=267) | Paclitaxel (N=262)
Median age (years) | 53 | 52
Range | 26 to 83 | 26 to 75
Metastatic disease | 97% | 97%
Baseline KPSa≥90 | 70% | 74%
Number of tumor sites
1-2 | 57% | 59%
≥3 | 43% | 41%
Visceral disease | 73% | 73%
Prior anthracycline | 97% | 96%
aKarnofsky Performance Status

Table 19: Efficacy Results in Study 2
Efficacy Parameter | Gemcitabine/Paclitaxel (N=267) |  | Paclitaxel (N=262)
Time to Documented Disease Progressiona
Median (95% CI) in months | 5.2 (4.2, 5.6) |  | 2.9 (2.6, 3.7)
Hazard Ratio (95% CI) | 0.650 (0.524, 0.805)
p-value | p<0.0001
Overall Survivalb
Median Survival (95% CI) in months | 18.6 (16.5, 20.7) |  | 15.8 (14.1, 17.3)
Hazard Ratio (95% CI) | 0.86 (0.71, 1.04)
p-value | Not Significant
Overall Response Rate | 40.8% |  | 22.1%
(95% CI) | (34.9, 46.7) |  | (17.1, 27.2)
p-value | p<0.0001
bThese represent reconciliation of investigator and Independent Review Committee assessments according to a predefined algorithm.
cBased on the ITT population.

Figure 2: Kaplan-Meier Curves for Time to Documented Disease Progression in Study 2

14.3 Non-Small Cell Lung Cancer

The efficacy of gemcitabine was evaluated in two randomized, multicenter trials.

Study 3: 28-Day Schedule

A multinational, randomized trial (Study 3) compared gemcitabine with cisplatin to cisplatin alone in the treatment of patients with inoperable Stage IIIA, IIIB, or IV NSCLC who had not received prior chemotherapy. Patients were randomized to receive either gemcitabine 1000 mg/m2 on Days 1, 8, and 15 of each 28-day cycle with cisplatin 100 mg/m2 on Day 1 after gemcitabine administration (N=260) or cisplatin 100 mg/m2 on Day 1 of each 28-day cycle (N=262). The major efficacy outcome measure was overall survival.

A total of 522 patients were enrolled. Demographics and baseline characteristics (Table 20) were similar between arms with the exception of histologic subtype of NSCLC, with 48% of patients on the cisplatin arm and 37% of patients on the gemcitabine with cisplatin arm having adenocarcinoma.

Efficacy results are presented in Table 21and Figure 3.

Study 4: 21-Day Schedule

A randomized (1:1), multicenter trial (Study 4) was conducted in patients with Stage IIIB or IV NSCLC. Patients were randomized to receive either gemcitabine 1250 mg/m^2on Days 1 and 8 of each 21-day cycle with cisplatin 100 mg/m^2on Day 1 after gemcitabine administration or etoposide 100 mg/m^2intravenously on Days 1, 2, and 3 with cisplatin 100 mg/m^2on Day 1 of each 21 -day cycle. The major efficacy outcome measure was response rate.

A total of 135 patients were enrolled. Demographics and baseline characteristics are summarized in Table 20.

Efficacy results are presented in Table 21. There was no significant difference in survival between the two treatment arms. The median survival was 8.7 months for the gemcitabine with cisplatin arm versus 7 months for the etoposide with cisplatin arm. Median time to disease progression for the gemcitabine with cisplatin arm was 5 months compared to 4.1 months on the etoposide with cisplatin arm (Log-rank p=0.015, two-sided). The objective response rate for the gemcitabine with cisplatin arm was 33% compared to 14% on the etoposide with cisplatin arm (Fisher’s Exact p=0.01, two-sided).

Table 20: Baseline Demographics and Clinical Characteristics for Studies 3 and 4
Trial | 28-day Schedule (Study 3) |  | 21-day Schedule (Study 4)
 | Gemcitabine/Cisplatin (N=260) | Cisplatin (N=262) | Gemcitabine/Cisplatin (N=69) | Etoposide/ Cisplatin (N=66)
Male | 70% | 71% | 93% | 92%
Median age, years | 62 | 63 | 58 | 60
Range | 36 to 88 | 35 to 79 | 33 to 76 | 35 to 75
Stage IIIA | 7% | 7% | N/Aa | N/Aa
Stage IIIB | 26% | 23% | 48% | 52%
Stage IV | 67% | 70% | 52% | 49%
Baseline KPSb70 to 80 | 41% | 44% | 45% | 52%
Baseline KPSb90 to 100 | 57% | 55% | 55% | 49%
aN/A Not Applicable
bKarnofsky Performance Status.

Table 21: Efficacy Results for Studies 3 and 4
Trial | 28-day Schedule (Study 3) |  | 21-day Schedule (Study 4)
Efficacy Parameter | Gemcitabine/Cisplatin | Cisplatin | Gemcitabine/Cisplatin | Etoposide/Cisplatin
Survival
Median (95% CIa) in months | 9.0 (8.2, 11.0) | 7.6 (6.6, 8.8) | 8.7 (7.8, 10.1) | 7.0 (6.0, 9.7)
p-valueb | p=0.008 |  | p=0.18
Time to Disease Progression
Median (95% CIa)in months | 5.2 (4.2, 5.7) | 3.7 (3.0, 4.3) | 5.0 (4.2, 6.4) | 4.1 (2.4, 4.5)
p-valueb | p=0.009 |  | p=0.015
Tumor Response | 26% | 10% | 33% | 14%
p-valueb | p<0.0001 |  | p=0.01
aCI=confidence intervals
bp-value two-sided Fisher’s Exact test for difference in binomial proportions; log-rank test for time-to-event analyses.

Figure 3: Kaplan-Meier Survival Curves in Study 3

14.4 Pancreatic Cancer

The efficacy of gemcitabine was evaluated in two trials (Studies 5 and 6), a randomized, single-blind, two-arm, active-controlled trial (Study 5) conducted in patients with locally advanced or metastatic pancreatic cancer who had received no prior chemotherapy and in a single-arm, open-label, multicenter trial (Study 6) conducted in patients with locally advanced or metastatic pancreatic cancer previously treated with fluorouracil or a fluorouracil-containing regimen. In Study 5, patients were randomized to receive either gemcitabine 1000 mg/min^2intravenously over 30 minutes once weekly for 7 weeks followed by a one-week rest, then once weekly for 3 consecutive weeks every 28-days in subsequent cycles (n=63) or fluorouracil 600 mg/m^2intravenously over 30 minutes once weekly (n=63). In Study 6, all patients received gemcitabine 1000 mg/m^2intravenously over 30 minutes once weekly for 7 weeks followed by a one-week rest, then once weekly for 3 consecutive weeks every 28-days in subsequent cycles.

The major efficacy outcome measure in both trials was “clinical benefit response”. A patient was considered to have had a clinical benefit response if either of the following occurred:

- The patient achieved a ≥50% reduction in pain intensity (Memorial Pain Assessment Card) or analgesic consumption, or a 20-point or greater improvement in performance status (Karnofsky Performance Status) for a period of at least 4 consecutive weeks, without showing any sustained worsening in any of the other parameters. Sustained worsening was defined as 4 consecutive weeks with either any increase in pain intensity or analgesic consumption or a 20-point decrease in performance status occurring during the first 12 weeks of therapy.

OR

- The patient was stable on all of the aforementioned parameters and showed a marked, sustained weight gain (≥7% increase maintained for ≥4 weeks) not due to fluid accumulation.

Study 5 enrolled 126 patients. Demographics and baseline characteristics were similar between the arms (Table 22).

The efficacy results are shown in Table 23and Figure 4. Patients treated with gemcitabine had statistically significant increases in clinical benefit response, survival, and time to disease progression compared to those randomized to receive fluorouracil. No confirmed objective tumor responses were observed in either treatment arm.

Table 22: Baseline Demographics and Clinical Characteristics for Study 5
 | Gemcitabine (N= 63) | Fluorouracil (N= 63)
Male | 54% | 54%
Median age, years | 62 | 61
Range | 37 to 79 | 36 to 77
Stage IV disease | 71% | 76%
Baseline KPSa≤70 | 70% | 68%
aKarnofsky Performance Status.

Table 23: Efficacy Results in Study 5
Efficacy Parameter | Gemcitabine (N= 63) | Fluorouracil (N= 63)
Clinical Benefit Response | 22.2% | 4.8%
p-valuea | p=0.004
Survival
Median (95% CI) in months | 5.7 (4.7, 6.9) | 4.2 (3.1, 5.1)
p-valuea | p=0.0009
Time to Disease Progression
Median (95% CI) in months | 2.1 (1.9, 3.4) | 0.9 (0.9, 1.1)
p-valuea | p=0.0013
ap-value for clinical benefit response calculated using the two-sided test for difference in binomial proportions. All other p- values are calculated using log-rank test.

Figure 4: Kaplan-Meier Curves for Overall Survival in Study 5

15 REFERENCES

1.“OSHA Hazardous Drugs. ”OSHA. http://www.osha.gov/SLTC/hazardousdrugs/index.html

16 HOW SUPPLIED/STORAGE AND HANDLING

Gemcitabine Injection is a clear colorless to pale yellow solution available in sterile multiple-dose vials containing:

Vial | NDC number
200 mg/2 mL (100 mg/mL) 1 g/10 mL (100 mg/mL) 1.5 g/15 mL (100 mg/mL) 2 g/ 20 mL (100 mg/mL) | 16729-391-30 16729-419-03 16729-423-33 16729-426-05

Store at 20°C to 25°C (68°F to 77°F); excursions permitted between 15° C and 30°C (59°F and 86°F) [see USP Controlled Room Temperature].

After initial puncture, Gemcitabine Injection multiple-dose vials are stable for 28 days when stored at room temperature.

Gemcitabine Injection is a cytotoxic drug. Follow applicable special handling and disposal procedures.^1

17 PATIENT COUNSELING INFORMATION

Myelosuppression

Advise patients of the risks of myelosuppression. Instruct patients to immediately contact their healthcare provider should any signs or symptoms of infection, including fever, or if bleeding or signs of anemia, occur [see Warnings and Precautions (5.2)].

Severe Cutaneous Adverse Reactions (SCARs)

Advise patients of the risks of SCARs, including Stevens-Johnson syndrome (SJS), toxic epidermal necrolysis (TEN), drug reaction with eosinophilia and systemic symptoms (DRESS), and acute generalized exanthematous pustulosis (AGEP). Instruct patients to immediately contact their healthcare provider should any signs or symptoms of severe skin rash or skin peeling, blistering and/or mouth sores occur [see Warnings and Precautions (5.3)].

Pulmonary Toxicity

Advise patients of the risks of pulmonary toxicity, including respiratory failure and death. Instruct patients to immediately contact their healthcare provider for development of shortness of breath, wheezing, or cough [see Warnings and Precautions (5.4)].

Hemolytic Uremic Syndrome and Renal Failure

Advise patients of the risks of hemolytic uremic syndrome and associated renal failure. Instruct patients to immediately contact their healthcare provider for changes in the color or volume of urine output or for increased bruising or bleeding [see Warnings and Precautions (5.5)].

Hepatic Toxicity

Advise patients of the risks of hepatic toxicity including liver failure and death. Instruct patients to immediately contact their healthcare provider for signs of jaundice or for pain/tenderness in the right upper abdominal quadrant [see Warnings and Precautions (5.6)].

Embryo-Fetal Toxicity

Advise females and males of reproductive potential that Gemcitabine Injection can cause fetal harm. Advise females of reproductive potential to use effective contraception during treatment with Gemcitabine Injection and for 6 months after the final dose. Advise male patients with female partners of reproductive potential to use effective contraception during treatment with Gemcitabine Injection and for 3 months after the final dose [see Warnings and Precaution (5.7), Use in Specific Populations (8.1, 8.3)].

Lactation

Advise women not to breastfeed during treatment with Gemcitabine Injection and for at least one week after the last dose [see Use in Specific Populations (8.2)].

Infertility

Advise males of reproductive potential of the potential for reduced fertility with Gemcitabine Injection [see Use in Specific Populations (8.3), Nonclinical Toxicology (13.1)].

Manufactured For:
Accord Healthcare, Inc.,
8041 Arco Corporate Drive,
Suite 200,
Raleigh, NC 27617,
USA.

Manufactured By:
Intas Pharmaceuticals Limited,
Ahmedabad-380 054, India.

10 3044 4 6030546

Issued September 2024

PACKAGE CARTON – 200 mg/2 mL

PACKAGE CONTAINER – 200 mg/2 mL

PACKAGE CARTON – 1 g/10 mL

PACKAGE CONTAINER – 1 g/10 mL

PACKAGE CARTON – 1.5 g/15 mL

PACKAGE CONTAINER – 1.5 g/15 mL

PACKAGE CARTON – 2 g/20 mL

PACKAGE CONTAINER – 2 g/20 mL